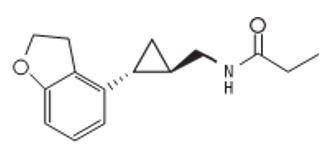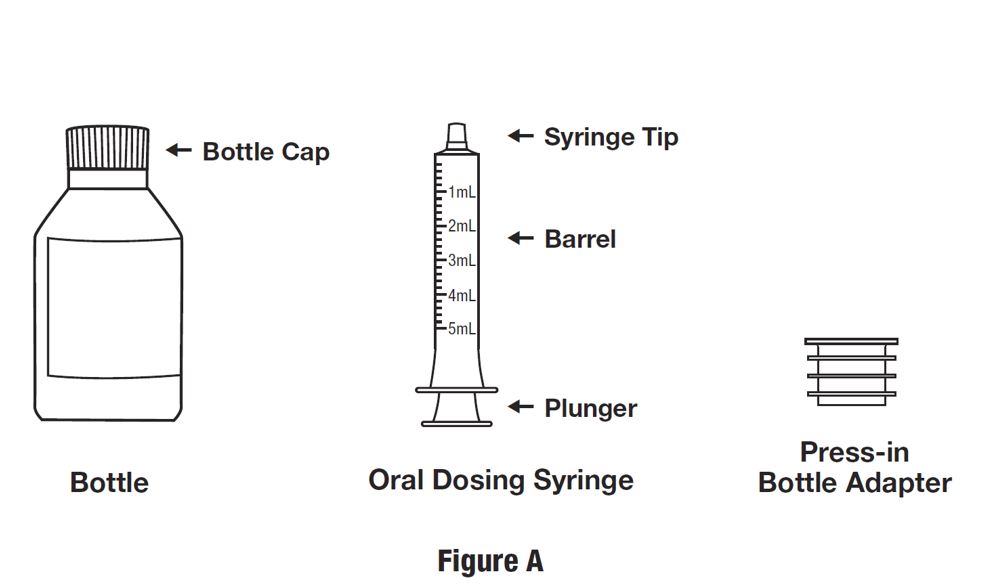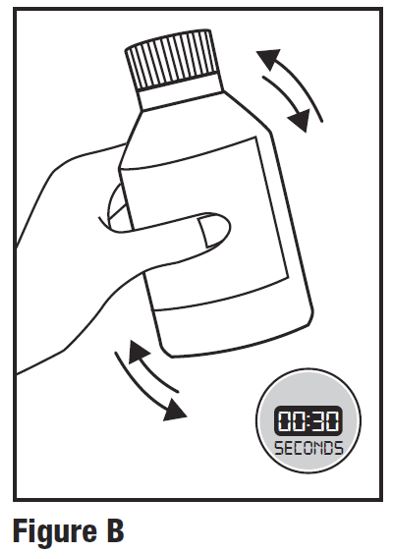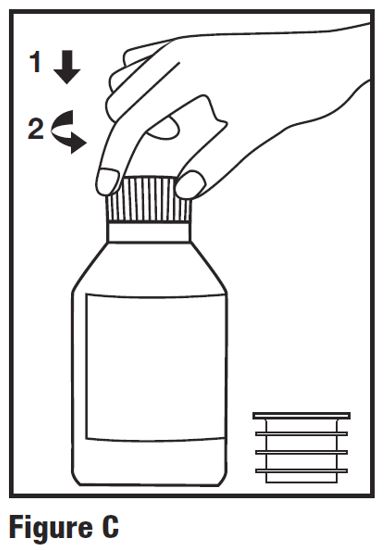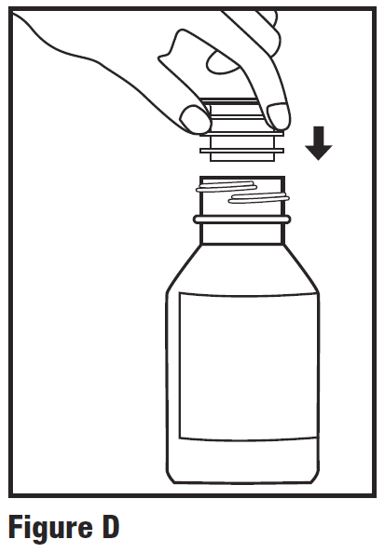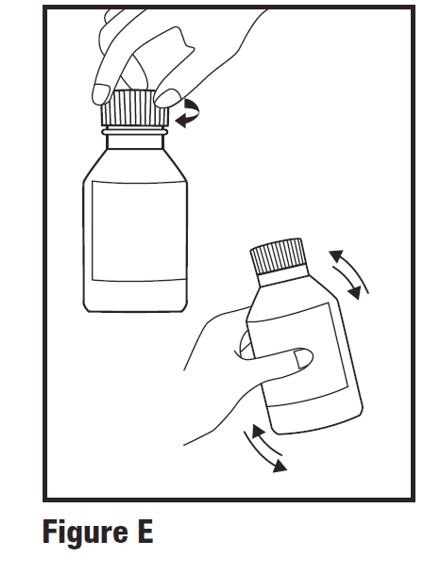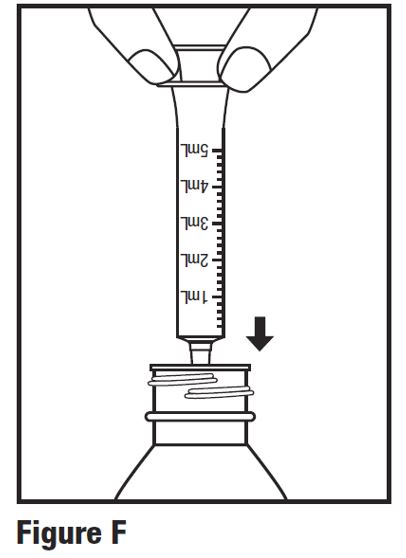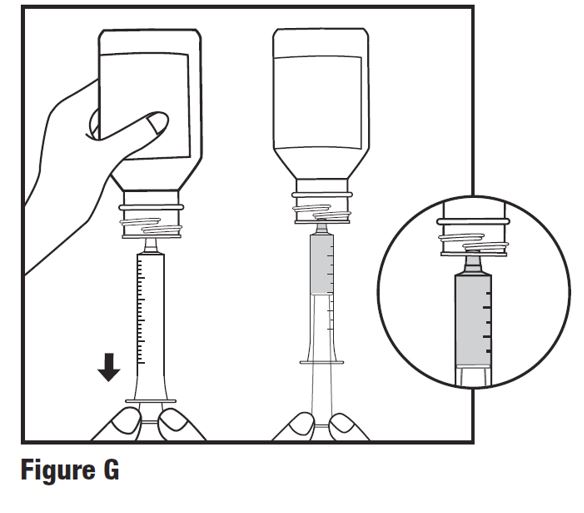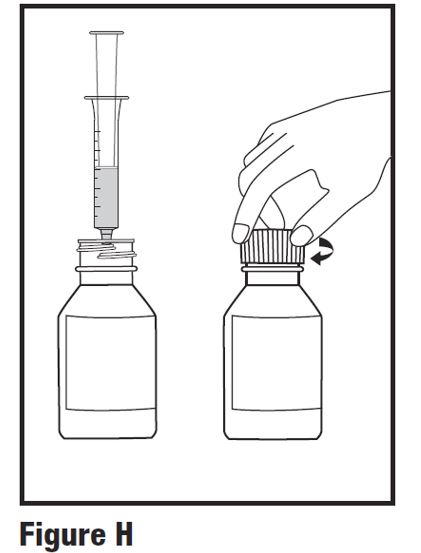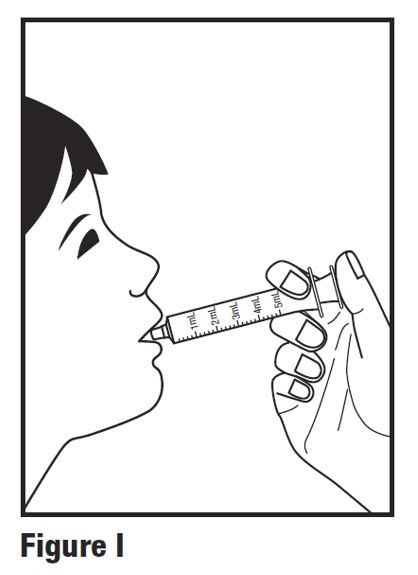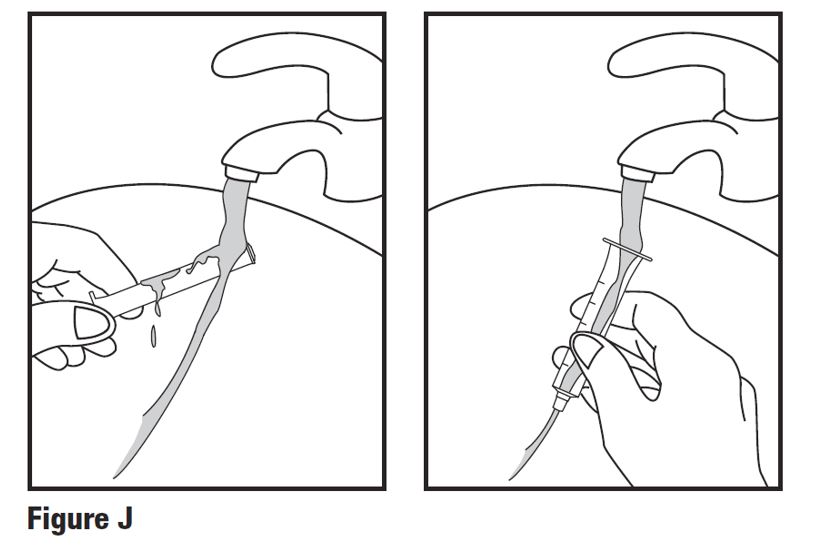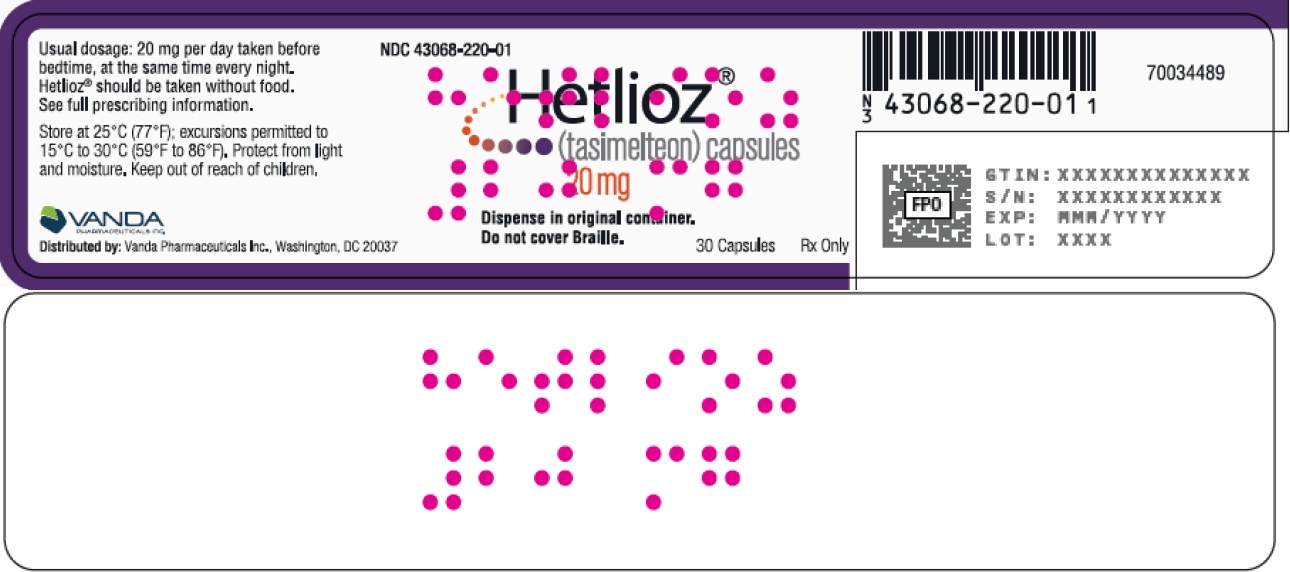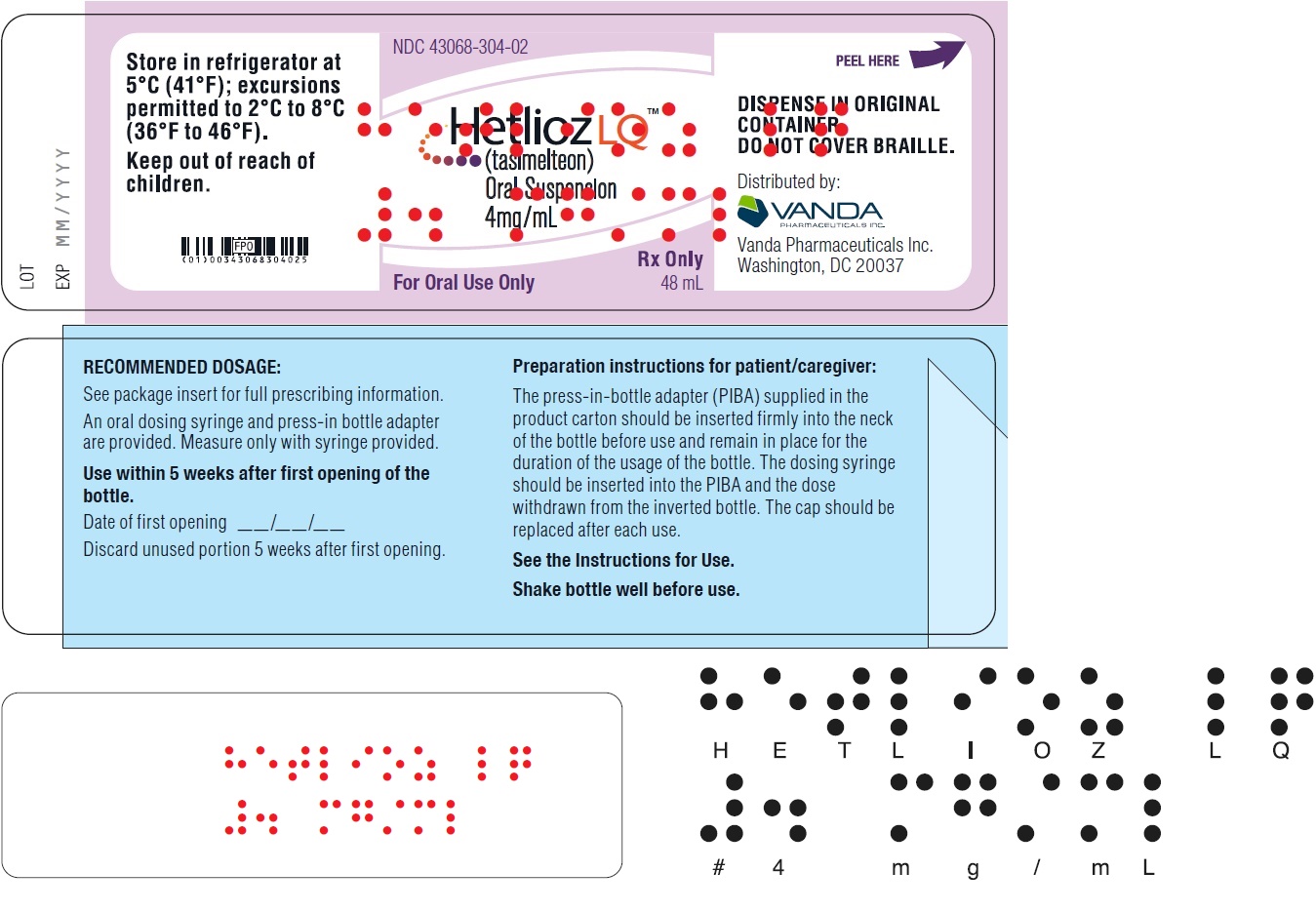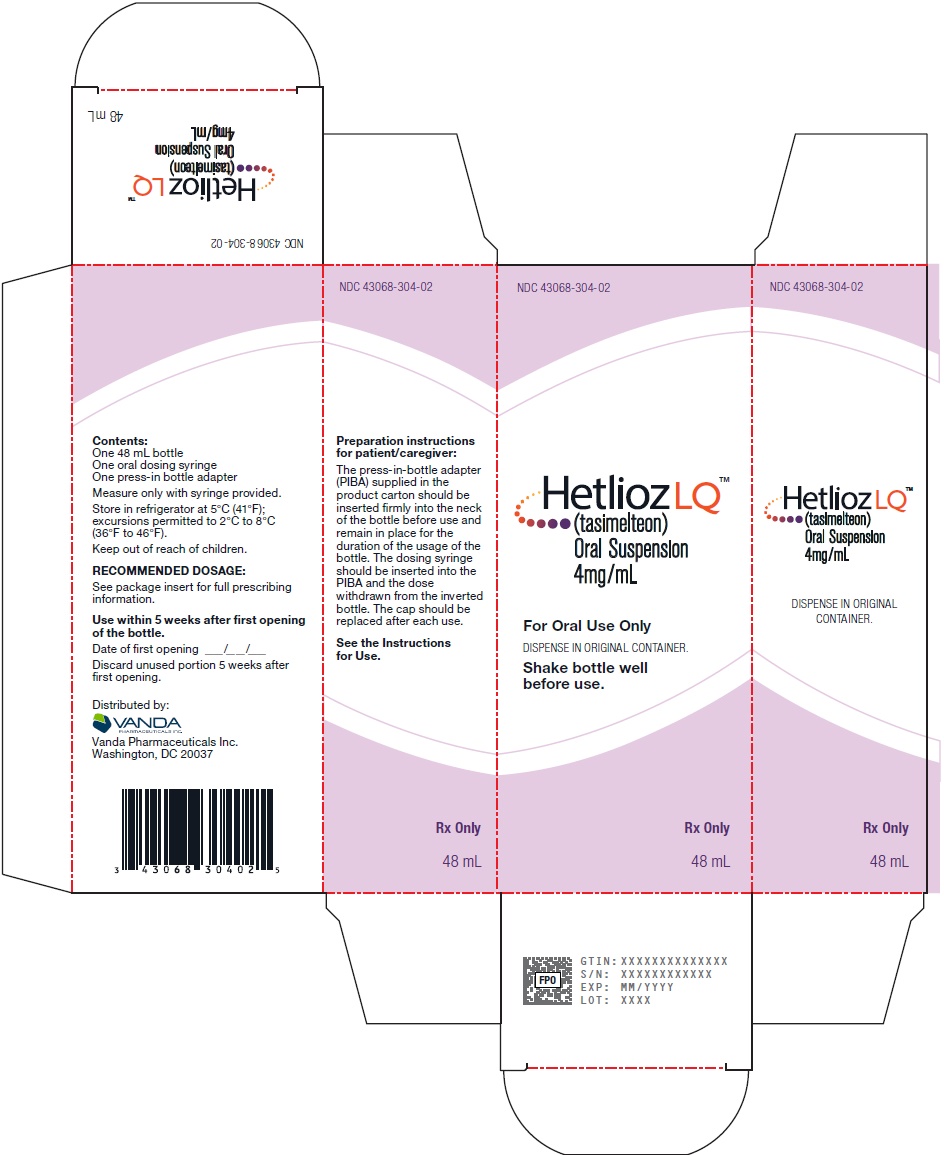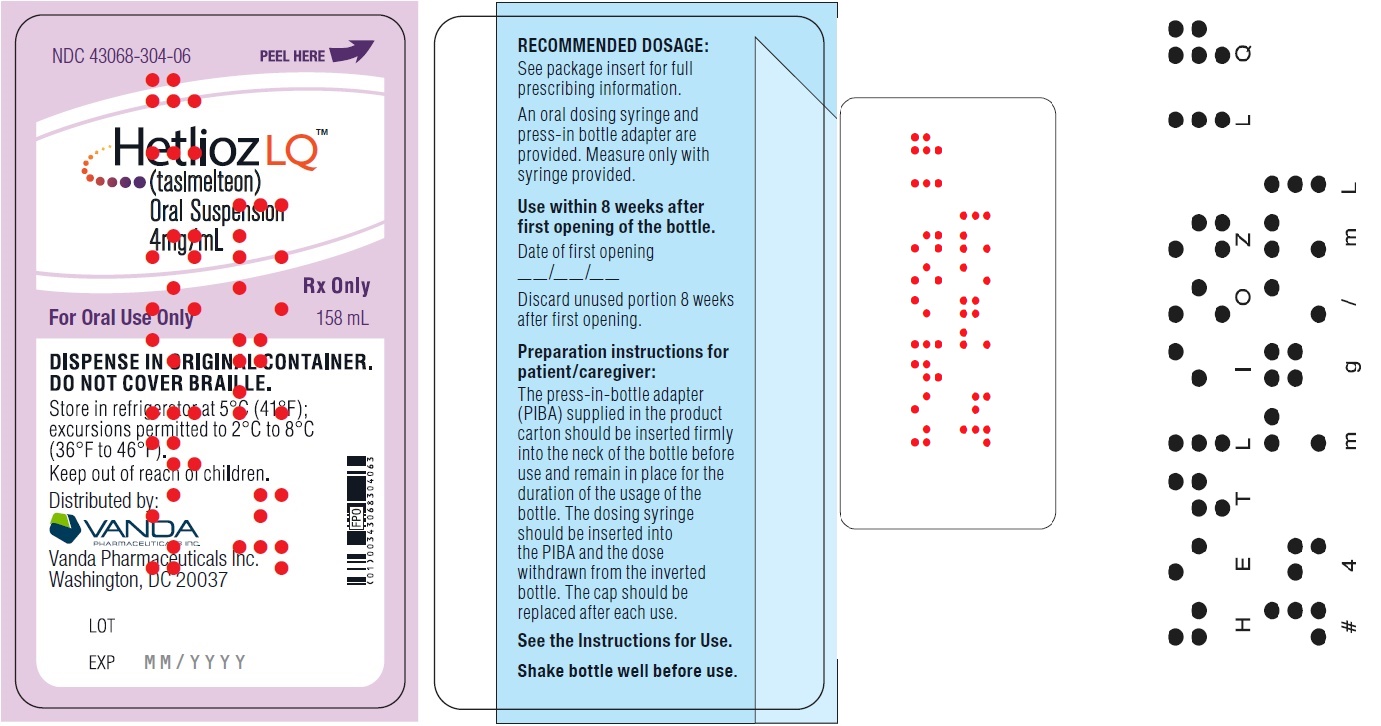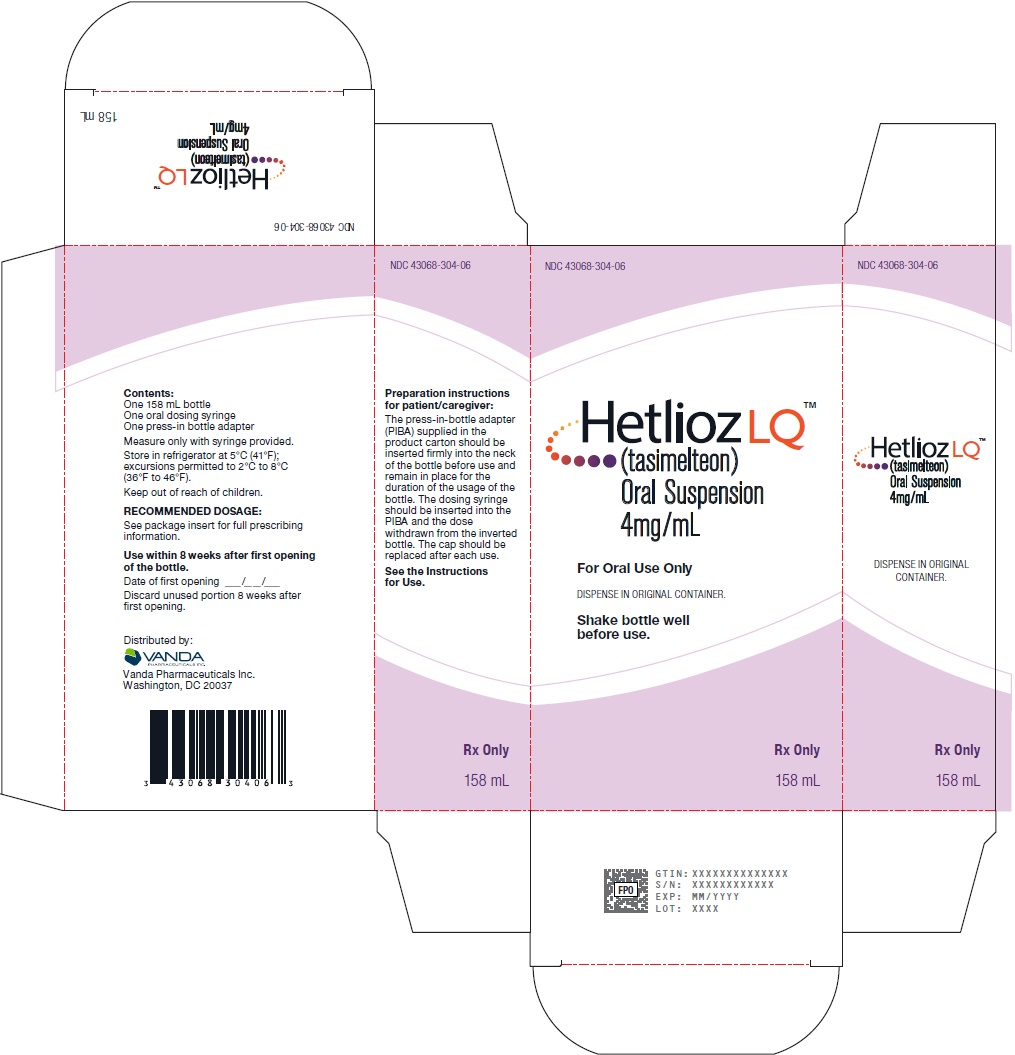 DRUG LABEL: Hetlioz
NDC: 43068-220 | Form: CAPSULE
Manufacturer: Vanda Pharmaceuticals Inc.
Category: prescription | Type: HUMAN PRESCRIPTION DRUG LABEL
Date: 20221221

ACTIVE INGREDIENTS: TASIMELTEON 20 mg/1 1
INACTIVE INGREDIENTS: ANHYDROUS LACTOSE; MICROCRYSTALLINE CELLULOSE; CROSCARMELLOSE SODIUM; SILICON DIOXIDE; MAGNESIUM STEARATE; FD&C BLUE NO. 1; FD&C RED NO. 3; FD&C YELLOW NO. 6; TITANIUM DIOXIDE; GELATIN, UNSPECIFIED

HIGHLIGHTS OF PRESCRIBING INFORMATION

These highlights do not include all the information needed to use HETLIOZ safely and effectively. See full prescribing information for HETLIOZ.
HETLIOZ® (tasimelteon) capsules, for oral use
HETLIOZ LQ™ (tasimelteon) oral suspension
Initial U.S. Approval: 2014

RECENT MAJOR CHANGES

Indications and Usage (1) | 12/2020
Dosage and Administration (2.1, 2.3, 2.4) | 12/2020

1 INDICATIONS AND USAGE

HETLIOZ is a melatonin receptor agonist.

- HETLIOZ capsules are indicated for the treatment of:
- Non-24-Hour Sleep-Wake Disorder (Non-24) in adults (1)
- Nighttime sleep disturbances in Smith-Magenis Syndrome (SMS) in patients 16 years of age and older (1)

HETLIOZ LQ oral suspension is indicated for the treatment of:

- Nighttime sleep disturbances in SMS in pediatric patients 3 years to 15 years of age (1)

2 DOSAGE AND ADMINISTRATION

Indicated Population | Dosage Form | Body Weight | Recommended Dosage
Non-24 (2.2)
Adults | Capsules | Not applicable | 20 mg one hour prior to bedtime
Nighttime sleep disturbances in SMS (2.3)
Patients 16 years of age and older | Capsules | Not applicable | 20 mg one hour prior to bedtime
Pediatric Patients 3 to 15 years of age | Oral Suspension | ≤ 28 kg | 0.7 mg/kg one hour before bedtime
Pediatric Patients 3 to 15 years of age | Oral Suspension | ≥ 28 kg | 20 mg one hour prior to bedtime

- HETLIOZ capsules and HETLIOZ LQ oral suspension are not substitutable (2.1)
- Administer at the same time every night (2.2, 2.3)
- Take without food (2.4)

3 DOSAGE FORMS AND STRENGTHS

- Capsules: 20 mg (3)
- Oral Suspension: 4 mg/mL (3)

4 CONTRAINDICATIONS

None (4)

5 WARNINGS AND PRECAUTIONS

May cause somnolence: After taking HETLIOZ, patients should limit their activity to preparing for going to bed, because HETLIOZ can impair the performance of activities requiring complete mental alertness (5.1)

6 ADVERSE REACTIONS

The most common adverse reactions (incidence >5% and at least twice as high on HETLIOZ than on placebo) were headache, increased alanine aminotransferase, nightmares or unusual dreams, and upper respiratory or urinary tract infection (6.1)

To report SUSPECTED ADVERSE REACTIONS, contact Vanda Pharmaceuticals Inc. at 1-844-438-5469 or www.hetlioz.com or FDA at 1-800-FDA-1088 or www.fda.gov/medwatch.

7 DRUG INTERACTIONS

- Strong CYP1A2 inhibitors (e.g., fluvoxamine): Avoid use of HETLIOZ in combination with strong CYP1A2 inhibitors because of increased exposure (7.1, 12.3)
- Strong CYP3A4 inducers (e.g., rifampin): Avoid use of HETLIOZ in combination with rifampin or other CYP3A4 inducers, because of decreased exposure (7.2, 12.3)

8 USE IN SPECIFIC POPULATIONS

Hepatic impairment: HETLIOZ has not been studied in patients with severe hepatic impairment and is not recommended in these patients (8.6)

FULL PRESCRIBING INFORMATION

1 INDICATIONS AND USAGE

1.1 Non-24-Hour Sleep-Wake Disorder (Non-24)

- HETLIOZ capsules are indicated for the treatment of Non-24 in adults.

1.2 Nighttime Sleep Disturbances in Smith-Magenis Syndrome (SMS)

- HETLIOZ capsules are indicated for the treatment of nighttime sleep disturbances in SMS in patients 16 years of age and older.
- HETLIOZ LQ oral suspension is indicated for the treatment of nighttime sleep disturbances in SMS in pediatric patients 3 to 15 years of age.

2 DOSAGE AND ADMINISTRATION

2.1 Non-Interchangeability between HETLIOZ Capsules and HETLIOZ LQ Oral Suspension

HETLIOZ capsules and HETLIOZ LQ oral suspension are not substitutable [see Clinical Pharmacology (12.3)].

2.2 Recommended Dosage for HETLIOZ Capsules for Non-24

Adults
The recommended dosage of HETLIOZ capsules in adults is 20 mg one hour before bedtime, at the same time every night.

Because of individual differences in circadian rhythms, drug effect may not occur for weeks or months.

2.3 Recommended Dosage for HETLIOZ Capsules and HETLIOZ LQ Oral Suspension for Nighttime Sleep Disturbances in SMS

Patients 16 years of Age and Older
The recommended dosage of HETLIOZ capsules in patients 16 years and older is 20 mg one hour before bedtime, at the same time every night.

Pediatric Patients 3 Years to 15 Years of Age
The recommended dosage of HETLIOZ LQ oral suspension in pediatric patients 3 years to 15 years of age is based on body weight (Table 1). Administer HETLIOZ one hour before bedtime, at the same time every night.

Table 1: Recommended Dosage of HETLIOZ LQ Oral Suspension for the Treatment of Nighttime Sleep Disturbances in SMS in Pediatric Patients 3 Years to 15 Years of Age
Body Weight | Daily Dose (oral suspension)
≤28 kg | 0.7 mg/kg one hour before bedtime
>28 kg | 20 mg one hour before bedtime

2.4 Important Administration Information

Administer HETLIOZ capsules and HETLIOZ LQ oral suspension without food [see Clinical Pharmacology (12.3)].

If a patient is unable to take HETLIOZ at approximately the same time on a given night, they should skip that dose and take the next dose as scheduled.

HETLIOZ LQ Oral Suspension

See "Instructions for Use" for complete administration instructions.

Shake HETLIOZ LQ oral suspension well for at least 30 seconds before every administration. Remove seal and insert press-in bottle adapter (included in the package) into the neck of the bottle until a tight seal is made. Turn the bottle upside down and withdraw the prescribed amount of HETLIOZ LQ oral suspension from the bottle. Leave the press-in bottle adapter in place on bottle neck and replace cap on bottle. Store refrigerated. After opening, discard after 5 weeks (for the 48 mL bottle) and after 8 weeks (for the 158 mL bottle).

3 DOSAGE FORMS AND STRENGTHS

Capsules: 20 mg size 1 dark blue opaque, hard gelatin capsules printed with “VANDA 20 mg” in white.

Oral suspension: 4 mg/mL white to slightly yellow opaque suspension in 48 mL or 158 mL bottles.

4 CONTRAINDICATIONS

None.

5 WARNINGS AND PRECAUTIONS

5.1 Somnolence

After taking HETLIOZ, patients should limit their activity to preparing for going to bed. HETLIOZ can potentially impair the performance of activities requiring complete mental alertness.

6 ADVERSE REACTIONS

6.1 Clinical Trials Experience

Because clinical trials are conducted under widely varying conditions, adverse reaction rates observed in the clinical trials of a drug cannot be directly compared to rates in the clinical trials of another drug and may not reflect the rates observed in clinical practice.

More than 2080 subjects have been treated with at least one dose of HETLIOZ, of which more than 380 have been treated for > 26 weeks and more than 170 have been treated for > 1 year.

Non-24-Hour Sleep-Wake Disorder (Non-24)
A 26-week, parallel-arm placebo-controlled study (Study 1) evaluated HETLIOZ (n=42) compared to placebo (n=42) in patients with Non-24. A randomized-withdrawal, placebo- controlled study of 8 weeks duration (Study 2) also evaluated HETLIOZ (n=10), compared to placebo (n=10), in patients with Non-24.

In placebo-controlled studies, 6% of patients exposed to HETLIOZ discontinued treatment due to an adverse event, compared with 4% of patients who received placebo.

Table 2 shows the incidence of adverse reactions from Study 1.

Table 2: Adverse Reactions in Study 1
 | HETLIOZ N=42 | Placebo N=42
Headache | 17 % | 7 %
Alanine aminotransferase increased | 10 % | 5 %
Nightmare/abnormal dreams | 10 % | 0 %
Upper respiratory tract infection | 7 % | 0 %
Urinary tract infection | 7 % | 2 %
*Adverse reactions with an incidence > 5% and at least twice as high on HETLIOZ than on placebo are displayed.

Nighttime Sleep Disturbances in Smith-Magenis Syndrome (SMS)
A 9-week, double-blind, randomized, placebo-controlled, two-period crossover study evaluated HETLIOZ (capsules and oral suspension; n=25) compared to placebo (n=26) in the treatment of nighttime sleep disturbances in patients with Smith-Magenis Syndrome. Pediatric patients (n=11, age 3 to 15 years) received HETLIOZ LQ oral suspension, and patients ≥16 years of age (n=14) received HETLIOZ capsules.

Adverse reactions were similar in patients treated for Non-24 and patients with Smith-Magenis syndrome treated for nighttime sleep disturbances. Adverse reactions were also similar in pediatric patients (3 years to 15 years) who received HETLIOZ LQ oral suspension, and patients ≥16 years of age who received HETLIOZ capsules.

7 DRUG INTERACTIONS

7.1 Strong CYP1A2 Inhibitors (e.g., fluvoxamine)

Avoid use of HETLIOZ in combination with fluvoxamine or other strong CYP1A2 inhibitors because of a potentially large increase in tasimelteon exposure and greater risk of adverse reactions [see Clinical Pharmacology (12.3)].

7.2 Strong CYP3A4 Inducers (e.g., rifampin)

Avoid use of HETLIOZ in combination with rifampin or other CYP3A4 inducers because of a potentially large decrease in tasimelteon exposure with reduced efficacy [see Clinical Pharmacology (12.3)].

7.3 Beta-adrenergic Receptor Antagonists (e.g., acebutolol, metoprolol)

Beta-adrenergic receptor antagonists have been shown to reduce the production of melatonin via specific inhibition of beta-1 adrenergic receptors. Nighttime administration of beta-adrenergic receptor antagonists may reduce the efficacy of HETLIOZ.

8 USE IN SPECIFIC POPULATIONS

8.1 Pregnancy

Risk Summary
Available postmarketing case reports with HETLIOZ use in pregnant women are not sufficient to evaluate drug-associated risk of major birth defects, miscarriage or adverse maternal or fetal outcomes. In pregnant rats, no embryofetal developmental toxicity was observed at exposures of 50 mg/kg/day, or up to 24 times higher than the human exposure at the maximum recommended human dose (MRHD) (see Data).

The estimated background risk of major birth defects and miscarriage for the indicated populations are unknown. In the U.S. general population, the estimated background risk of major birth defects and miscarriage in clinically recognized pregnancies is 2% to 4% and 15% to 20%, respectively.

Data
Animal Data
In pregnant rats administered tasimelteon at oral doses of 5, 50, or 500 mg/kg/day during the period of organogenesis, there were no effects on embryofetal development. The highest dose tested is approximately 240 times the MRHD of 20 mg/day, based on mg/m^2 body surface area.

In pregnant rabbits administered tasimelteon at oral doses of 5, 30, or 200 mg/kg/day during the period of organogenesis, embryolethality and embryofetal toxicity (reduced fetal body weight and delayed ossification) were observed at the highest dose tested. The highest dose is approximately 200 times the MRHD.

Oral administration of tasimelteon at 50, 150, or 450 mg/kg/day to rats throughout organogenesis resulted in persistent reductions in body weight, delayed sexual maturation, and physical development, and neurobehavioral impairment in offspring at the highest dose tested which is approximately 220 times the MRHD based on mg/m2 body surface area. Reduced body weight in offspring was also observed at the mid-dose. The no effect dose (NOEL), (50 mg/kg/day) is approximately 25 times the MRHD based on mg/m^2 body surface area.

8.2 Lactation

Risk Summary
There are no data on the presence of tasimelteon or its metabolites in human or animal milk, the effects on the breastfed infant, or the effects on milk production. The developmental and health benefits of breastfeeding should be considered along with the mother’s clinical need for HETLIOZ and any potential adverse effects on the breastfed infant from HETLIOZ or from the underlying maternal condition.

8.4 Pediatric Use

Safety and effectiveness of HETLIOZ for the treatment of Non-24 in pediatric patients have not been established.

Safety and effectiveness of HETLIOZ LQ oral suspension for the treatment of nighttime sleep disturbances in Smith-Magenis Syndrome (SMS) have been established in pediatric patients 3 years and older. Use is based on a placebo-controlled crossover study of pediatric and adult patients [see Clinical Studies (14.2)].

Safety and effectiveness of HETLIOZ for the treatment of nighttime sleep disturbances in SMS have not been established in patients younger than 3 years old.

Juvenile Animal Toxicity Data
Juvenile rats received oral doses of tasimelteon at 50, 150, or 450 mg/kg from weaning (day 21) through adulthood (day 90). These doses are approximately 12 to 108 times the maximum recommended human dose (MRHD) of 20 mg based on a mg/m^2 body surface area. Toxicity was observed mainly at the highest dose and included mortality (females only), tremors, unsteady gait, decrease in growth and development compared to controls. The former reflected as decreases in bone growth, bone mineral content, bone ossification, and a delay in attainment of sexual maturation. Tasimelteon had no effect on fertility, reproduction, or learning and memory. The No Observed Adverse Effect Level (NOAEL) is 150 mg/kg/day, which is approximately 178 times the MRHD based on AUC.

8.5 Geriatric Use

The risk of adverse reactions may be greater in elderly (>65 years) patients than younger patients because exposure to tasimelteon is increased by approximately 2-fold compared with younger patients.

8.6 Hepatic Impairment

Dose adjustment is not necessary in patients with mild or moderate hepatic impairment. HETLIOZ has not been studied in patients with severe hepatic impairment (Child-Pugh Class C). Therefore, HETLIOZ is not recommended for use in patients with severe hepatic impairment [see Clinical Pharmacology (12.3)].

8.7 Smokers

Smoking causes induction of CYP1A2 levels. The exposure of tasimelteon in smokers was lower than in non-smokers and therefore the efficacy of HETLIOZ may be reduced in smokers [see Clinical pharmacology (12.3)].

9 DRUG ABUSE AND DEPENDENCE

9.1 Controlled Substance

Tasimelteon is not a controlled substance under the Controlled Substances Act.

9.2 Abuse

Tasimelteon did not produce any abuse-related signals in animal behavioral studies. Rats did not self-administer tasimelteon, suggesting that the drug does not have rewarding properties. There were also no signs or symptoms indicative of abuse potential in clinical studies with HETLIOZ.

9.3 Dependence

Discontinuation of HETLIOZ in humans following chronic administration did not produce withdrawal signs. HETLIOZ does not appear to produce physical dependence.

10 OVERDOSAGE

There is limited premarketing clinical experience with the effects of an overdosage of HETLIOZ.

As with the management of any overdose, general symptomatic and supportive measures should be used, along with immediate gastric lavage where appropriate. Intravenous fluids should be administered as needed. Respiration, pulse, blood pressure, and other appropriate vital signs should be monitored, and general supportive measures employed.

While hemodialysis was effective at clearing HETLIOZ and the majority of its major metabolites in patients with renal impairment, it is not known if hemodialysis will effectively reduce exposure in the case of overdose.

As with the management of any overdose, the possibility of multiple drug ingestion should be considered. Contact a poison control center for current information on the management of overdose.

11 DESCRIPTION

HETLIOZ (contains tasimelteon) a melatonin receptor agonist, chemically designated as (1R, 2R)-N-[2-(2,3-dihydrobenzofuran-4-yl)cyclopropylmethyl]propanamide, containing two chiral centers. The molecular formula is C15H19NO2, and the molecular weight is 245.32. The structural formula is:

Tasimelteon is a white to off-white crystalline powder. It is very slightly soluble in cyclohexane, slightly soluble in water and 0.1 N hydrochloric acid, and freely soluble or very soluble in methanol, 95% ethanol, acetonitrile, isopropanol, polyethylene glycol 300, propylene glycol and ethyl acetate.

HETLIOZ capsules are intended for oral administration. Each capsule contains 20 mg of tasimelteon and the following inactive ingredients: colloidal silicon dioxide, croscarmellose sodium, lactose anhydrous, magnesium stearate, and microcrystalline cellulose. Each hard gelatin capsule consists of FD&C Blue #1, FD&C Red #3, and FD&C Yellow #6, gelatin, and titanium dioxide.

HETLIOZ LQ oral suspension contains 4 mg of tasimelteon per mL of suspension and the following inactive ingredients: ascorbic acid, cherry flavor, mannitol, microcrystalline cellulose/carboxymethylcellulose sodium, polysorbate 80, sodium benzoate, sodium chloride, sucrose, sucralose, and water.

12 CLINICAL PHARMACOLOGY

12.1 Mechanism of Action

The mechanism by which tasimelteon exerts its therapeutic effect in patients with Non-24 or nighttime sleep disturbances in SMS is unclear. However, tasimelteon is an agonist at melatonin MT1 and MT2 receptors which are thought to be involved in the control of circadian rhythms.

12.2 Pharmacodynamics

Tasimelteon is an agonist at MT1 and MT2 receptors with greater affinity for the MT2 as compared to the MT1 receptor (Ki = 0.304 nM and 0.07 nM, respectively). The major metabolites of tasimelteon have less than one-tenth of the binding affinity of the parent molecule for both the MT1 and MT2 receptors.

12.3 Pharmacokinetics

The pharmacokinetics of tasimelteon is linear over doses ranging from 3 to 300 mg (0.15 to 15 times the recommended daily dosage). The pharmacokinetics of tasimelteon and its metabolites did not change with repeated daily dosing.

Absorption

The absolute oral bioavailability is 38.3%. The peak concentration (Tmax) of tasimelteon capsule occurred approximately 0.5 to 3 hours after fasted oral administration.The Tmax of tasimelteon suspension occurred approximately 15 to 30 minutes after fasted oral administration.

The pharmacokinetic profile of oral suspension has not been directly compared to capsules; therefore, capsules are the only dosage form recommended for use in adults.

Effect of food

When administered with a high-fat meal, the Cmax of tasimelteon was 44% lower than when given in a fasted state, and the median Tmax was delayed by approximately 1.75 hours. Therefore, HETLIOZ should be taken without food.

Distribution

The apparent oral volume of distribution of tasimelteon at steady state in young healthy subjects is approximately 59 - 126 L. At therapeutic concentrations, tasimelteon is about 90% bound to proteins.

Metabolism

Tasimelteon is extensively metabolized. Metabolism of tasimelteon consists primarily of oxidation at multiple sites and oxidative dealkylation resulting in opening of the dihydrofuran ring followed by further oxidation to give a carboxylic acid. CYP1A2 and CYP3A4 are the major isozymes involved in the metabolism of tasimelteon.

Phenolic glucuronidation is the major phase II metabolic route.

Major metabolites had 13-fold or less activity at melatonin receptors compared to tasimelteon.

Elimination

Following oral administration of radiolabeled tasimelteon, 80% of total radioactivity was excreted in urine and approximately 4% in feces, resulting in a mean recovery of 84%. Less than 1% of the dose was excreted in urine as the parent compound.

The observed mean elimination half-life for tasimelteon is 1.3 ± 0.4 hours. The mean terminal elimination half-life ± standard deviation of the main metabolites ranges from 1.3 ± 0.5 to 3.7 ± 2.2.

Repeated once daily dosing with HETLIOZ does not result in changes in pharmacokinetic parameters or significant accumulation of tasimelteon.

Studies in Specific Populations

Elderly
  In elderly subjects, tasimelteon exposure increased by approximately two-fold compared with non-elderly adults.
Pediatric Patients
  Pharmacokinetic information in pediatric patients are available only for the oral suspension formulation. Body weight was found to have significant effect on the pharmacokinetics. The increase in body weight was associated with increase in tasimelteon clearance up to 28 kg. The average dose normalized Cmax and AUCinf at the recommended dose was 231 ng/mL and 310 ng.h/mL. No data are available in patients less than 3 years old.
Gender
  The mean overall exposure of tasimelteon was approximately 20-30% greater in female than in male subjects.
Race
  The effect of race on exposure of HETLIOZ was not evaluated.
Hepatic Impairment
  The pharmacokinetic profile of a 20 mg dose of HETLIOZ was compared among eight subjects with mild hepatic impairment (Child-Pugh Score ≥5 and ≤6 points), eight subjects with moderate hepatic impairment (Child-Pugh Score ≥7 and ≤9 points), and 13 healthy matched controls. Tasimelteon exposure was increased less than two-fold in subjects with moderate hepatic impairment. Therefore, no dose adjustment is needed in patients with mild or moderate hepatic impairment. HETLIOZ has not been studied in patients with severe hepatic impairment (Child-Pugh Class C) and is not recommended in these patients.
Renal Impairment
  The pharmacokinetic profile of a 20 mg dose of HETLIOZ was compared among eight subjects with severe renal impairment (estimated glomerular filtration rate [eGFR] ≤ 29 mL/min/1.73m^2), eight subjects with end-stage renal disease (ESRD) (GFR < 15 mL/min/1.73m^2) requiring hemodialysis, and sixteen healthy matched controls. There was no apparent relationship between tasimelteon CL/F and renal function, as measured by either estimated creatinine clearance or eGFR. Subjects with severe renal impairment had a 30% lower clearance, and clearance in subjects with ESRD was comparable to that of healthy subjects. No dose adjustment is necessary for patients with renal impairment.
Smokers (smoking is a moderate CYP1A2 inducer)
  Tasimelteon exposure decreased by approximately 40% in smokers, compared to non- smokers [see Use in Specific Populations (8.7)].

Drug Interaction Studies

No potential drug interactions were identified in in vitro studies with CYP inducers or inhibitors of CYP1A1, CYP1A2, CYP2B6, CYP2C9/2C19, CYP2E1, CYP2D6, and transporters including P-glycoprotein, OATP1B1, OATP1B3, OCT2, OAT1, and OAT3.
Effect of Other Drugs on HETLIOZ
Drugs that inhibit CYP1A2 and CYP3A4 are expected to alter the metabolism of tasimelteon.
  Fluvoxamine (strong CYP1A2 inhibitor): the AUC0-inf and Cmax of tasimelteon increased by 7-fold and 2-fold, respectively, when co-administered with fluvoxamine 50 mg (after 6 days of fluvoxamine 50 mg per day) [see Drug Interactions (7.1)].
  Ketoconazole (strong CYP3A4 inhibitor): tasimelteon exposure increased by approximately 50% when co-administered with ketoconazole 400 mg (after 5 days of ketoconazole 400 mg per day) [see Drug Interactions (7.2)].
  Rifampin (strong CYP3A4 and moderate CYP2C19 inducer): the exposure of tasimelteon decreased by approximately 90% when co-administered with rifampin 600 mg (after 11 days of rifampin 600 mg per day). Efficacy may be reduced when HETLIOZ is used in combination with strong CYP3A4 inducers, such as rifampin [see Drug Interactions (7.2)].
Effect of HETLIOZ on Other Drugs
  Midazolam (CYP3A4 substrate): Administration of HETLIOZ 20 mg once a day for 14 days did not produce any significant changes in the Tmax, Cmax, or AUC of midazolam or 1-OH midazolam. This indicates there is no induction of CYP3A4 by tasimelteon at this dose.
  Rosiglitazone (CYP2C8 substrate): Administration of HETLIOZ 20 mg once a day for 16 days did not produce any clinically significant changes in the Tmax, Cmax, or AUC of rosiglitazone after oral administration of 4 mg. This indicates that there is no induction of CYP2C8 by tasimelteon at this dose.
Effect of Alcohol on HETLIOZ
  In a study of 28 healthy volunteers, a single dose of ethanol (0.6 g/kg for women and 0.7 g/kg for men) was co-administered with a 20 mg dose of HETLIOZ. There was a trend for an additive effect of HETLIOZ and ethanol on some psychomotor tests.

13 NONCLINICAL TOXICOLOGY

13.1 Carcinogenesis, Mutagenesis, Impairment of Fertility

Carcinogenesis

Tasimelteon was administered orally for up to two years to mice (30, 100, and 300 mg/kg/day) and rats (20, 100, and 250 mg/kg/day). No evidence of carcinogenic potential was observed in mice; the highest dose tested is approximately 75 times the maximum recommended human dose (MRHD) of 20 mg/day, based on a mg/m^2body surface area. In rats, the incidence of liver tumors was increased in males (adenoma and carcinoma) and females (adenoma) at 100 and 250 mg/kg/day; the incidence of tumors of the uterus (endometrial adenocarcinoma) and uterus and cervix (squamous cell carcinoma) were increased at 250 mg/kg/day. There was no increase in tumors at the lowest dose tested in rats, which is approximately 10 times the MRHD based on a mg/m^2body surface area.

Mutagenesis

Tasimelteon was negative in an in vitro bacterial reverse mutation (Ames) assay, an in vitro cytogenetics assay in primary human lymphocytes, and an in vivo micronucleus assay in rats.

Impairment of Fertility

When male and female rats were given tasimelteon at oral doses of 5, 50, or 500 mg/kg/day prior to and throughout mating and continuing in females to gestation day 7, estrus cycle disruption and decreased fertility were observed at all but the lowest dose tested. The no-effect dose for effects on female reproduction (5 mg/kg/day) is approximately 2 times the MRHD based on a mg/m^2 body surface area.

14 CLINICAL STUDIES

14.1 Non-24-Hour Sleep-Wake Disorder (Non-24)

The effectiveness of HETLIOZ in the treatment of Non-24-Hour Sleep-Wake Disorder (Non-24) was established in two randomized double-masked, placebo-controlled, multicenter, parallel-group studies (Studies 1 and 2) in totally blind patients with Non-24.

In study 1, 84 patients with Non-24 (median age 54 years) were randomized to receive HETLIOZ 20 mg or placebo, one hour prior to bedtime, at the same time every night for up to 6 months.

Study 2 was a randomized withdrawal trial in 20 patients with Non-24 (median age 55 years) that was designed to evaluate the maintenance of efficacy of HETLIOZ after 12-weeks. Patients were treated for approximately 12 weeks with HETLIOZ 20 mg one hour prior to bedtime, at the same time every night. Patients in whom the calculated time of peak melatonin level (melatonin acrophase) occurred at approximately the same time of day (in contrast to the expected daily delay) during the run-in phase were randomized to receive placebo or continue treatment with HETLIOZ 20 mg for 8 weeks.

Study 1 and Study 2 evaluated the duration and timing of nighttime sleep and daytime naps via patient-recorded diaries. During Study 1, patient diaries were recorded for an average of 88 days during screening, and 133 days during randomization. During Study 2, patient diaries were recorded for an average of 57 days during the run-in phase, and 59 days during the randomized-withdrawal phase.

Because symptoms of nighttime sleep disruption and daytime sleepiness are cyclical in patients with Non-24, with severity varying according to the state of alignment of the individual patient’s circadian rhythm with the 24-hour day (least severe when fully aligned, most severe when 12 hours out of alignment), efficacy endpoints for nighttime total sleep time and daytime nap duration were based on the 25% of nights with the least nighttime sleep, and the 25% of days with the most daytime nap time. In Study 1, patients in the HETLIOZ group had, at baseline, an average 195 minutes of nighttime sleep and 137 minutes of daytime nap time on the 25% of most symptomatic nights and days, respectively. Treatment with HETLIOZ resulted in a significant improvement, compared with placebo, for both of these endpoints in Study 1 and Study 2 (see Table 3).

Table 3: Effects of HETLIOZ 20 MG on Nighttime Sleep Time and Daytime Nap Time in Study 1 and Study 2
 | Study 1 |  | Study 2
Change from Baseline | HETLIOZ 20 MG N=42 | Placebo N=42 | HETLIOZ 20 MG N=10 | Placebo N=10
Nighttime sleep time on 25% most symptomatic nights (minutes) | 50 | 22 | -7 | -74
Daytime nap time on 25% most symptomatic days (minutes) | -49 | -22 | -9 | 50

A responder analysis of patients with both ≥ 45 minutes increase in nighttime sleep and ≥ 45 minutes decrease in daytime nap time was conducted in Study 1: 29% (n=12) of patients treated with HETLIOZ, compared with 12% (n=5) of patients treated with placebo met the responder criteria.

14.2 Nighttime Sleep Disturbances in Smith-Magenis Syndrome (SMS)

The effectiveness of HETLIOZ in the treatment of nighttime sleep disturbances in Smith-Magenis Syndrome (SMS) was established in a 9-week, double-blind, placebo- controlled cross-over study in adults and pediatric patients with SMS (Study 3; NCT 02231008). Patients 16 years of age and older received HETLIOZ 20 mg capsules, and pediatric patients 3 years to 15 years of age received a weight-based dose of oral suspension.

Study 3 had two 4-week periods, separated by a 1-week washout interval. Patients were randomized to a treatment sequence of HELTIOZ in the first period and placebo in the second period, or placebo in the first period and HETLIOZ in the second period. Patients were to take the study drug one hour prior to bedtime.

The primary endpoints in Study 3 were nighttime total sleep time and nighttime sleep quality from a parent/guardian-recorded diary. Nighttime total sleep time was reported as a time unit in hours and minutes. Nighttime sleep quality was rated as follows: 5 = excellent; 4 = good; 3 = average; 2 = fair; 1 = poor. The efficacy comparisons for nighttime sleep quality and total sleep time were based on the 50% of nights with the worst sleep quality and the 50% of nights with the least nighttime sleep in each 4-week period. In accordance with the cross-over design, the efficacy comparisons were within patient.

A total of 25 patients were randomized in Study 3. During screening, the mean quality score of the 50% of nights with the worst sleep quality was 2.1, and the total sleep time of 50% of nights with the least nighttime sleep was 6.4 hours.

Compared to placebo, treatment with HETLIOZ resulted in a statistically significant improvement in the 50% worst nights’ sleep quality. Although improvement on the 50% worst total nighttime sleep time numerically favored HETLIOZ treatment, the difference was not statistically significant (Table 4).

Table 4: Primary Efficacy Results for Effects of HETLIOZ on Nighttime Sleep Quality and Nighttime Total Sleep Time in Patients with Smith-Magenis Syndrome (Study 3)
Primary Efficacy Measures | Treatment Group | LS Meana (SE) | Placebo-subtracted Differenceb (95% CI)
Average of 50% Worst Daily Nighttime Sleep Quality* | HETLIOZ (n=25) | 2.8 (0.15) | 0.4 (0.1, 0.7)
Average of 50% Worst Daily Nighttime Sleep Quality* | Placebo (n=25) | 2.4 (0.15) | --
Average of 50% Worst Daily Nighttime Total Sleep Time, hours | HETLIOZ (n=25) | 7.0 (0.26) | 0.3 (-0.0, 0.6)
Average of 50% Worst Daily Nighttime Total Sleep Time, hours | Placebo (n=25) | 6.7 (0.26) | --
SD: standard deviation; SE: standard error; LS Mean: least-squares mean; CI: confidence interval unadjusted for multiplicity.
aLS Means are the model-based averages based on the 50% worst days per 4-week period.
bDifference (drug minus placebo) in least-squares means.
*Endpoint on which HETLIOZ was statistically significant different from placebo after controlling for multiple comparisons.

16 HOW SUPPLIED/STORAGE AND HANDLING

HETLIOZ Capsules
20 mg capsules are available as size 1, dark blue opaque, hard gelatin capsules printed with “VANDA 20 mg” in white, containing 20 mg of tasimelteon per capsule.

- NDC 43068-220-01 Bottles of 30

HETLIOZ LQ Oral Suspension
4 mg/mL white to slightly yellow opaque suspension. Each bottle has a child resistant cap and packaged in a carton. Each carton contains a bottle of HETLIOZ LQ oral suspension, a 5 mL oral dosing syringe and a press-in bottle adapter.

- NDC 43068-304-02 Bottles of 48 mL
- NDC 43068-304-06 Bottles of 158 mL

Storage and Handling

HETLIOZ Capsules
Store HETLIOZ capsules at controlled room temperature, 20°C to25°C (68° to 77°F); excursions permitted to 15°C to 30°C (59°F to 86°F) [See USP Controlled Room Temperature]. Protect from exposure to light and moisture.

HETLIOZ LQ Oral Suspension
Store HETLIOZ LQ Oral suspension at refrigerated temperature 5°C (41°F); excursions permitted to 2°C to 8°C (36°F t o 46°F).

17 PATIENT COUNSELING INFORMATION

Advise the patient to read the FDA-approved patient labeling for HETLIOZ LQ oral suspension, if appropriate (Instructions for Use).

- Advise patients to limit their activities to preparing for going to bed after taking HETLIOZ capsules or HETLIOZ LQ oral suspension because HETLIOZ can potentially impair the performance of activities requiring complete mental alertness [see Warnings and Precautions (5.1)].
- Administration Information for HETLIOZ capsules and HETLIOZ LQ oral suspension [see Dosage and Administration (2.1, 2.2, 2.3, 2.4)].
  - Advise patients to take HETLIOZ without food.
  - Advise patients to take HETLIOZ before bedtime at the same time every night.
  - Advise patients to skip the dose that night if they cannot take HETLIOZ at approximately the same time on a given night.
  - Advise patients to swallow HETLIOZ capsules whole.
  - HETLIOZ LQ oral suspension:
    Advise patients to shake the bottle for at least 30 seconds before each administration; use the press-in bottle adapter included in the package; leave the adapter in place on the bottle neck; replace the cap; and refrigerate after each use. After opening, discard after 5 weeks (for the 48 mL bottle) and after 8 weeks (for the 158 mL bottle).
- Non-24 (HETLIOZ capsules)
  Advise patients that because of individual differences in circadian rhythms, daily use for several weeks or months may be necessary before benefit from HETLIOZ is observed [see Dosage and Administration (2.2)].

Distributed by:
Vanda Pharmaceuticals Inc.
Washington, D.C. 20037 USA
www.hetlioz.com

Vanda, HETLIOZ, and HETLIOZ LQ are trademarks or registered trademarks of Vanda Pharmaceuticals Inc. in the United States and other countries.

INSTRUCTIONS FOR USE

HETLIOZ LQ™ (HeT-lee-ōz eL-Cue)
(tasimelteon) oral suspension

Read this Instructions for Use before you give HETLIOZ LQ to your child and each time you get a refill. There may be new information. This leaflet does not take the place of talking to your healthcare provider about your medical condition or treatment.

Important information you need to know before giving HETLIOZ LQ to your child:

- Give HETLIOZ LQ exactly as your healthcare provider tells you to. Your healthcare provider will prescribe the dose of HETLIOZ that is right for your child based on body weight.
- Give HETLIOZ LQ one hour before bedtime, at the same time every night.
- Give HETLIOZ LQ without food.
- Skip the dose that night if you cannot give HETLIOZ LQ at about the same time on a given night.
- Limit your child’s activities to preparing for going to bed after taking HETLIOZ LQ because HETLIOZ LQ can potentially decrease mental alertness.
- People who have problems using their hands may need help to draw up and give the correct dose of HETLIOZ LQ.
- Write the date that you first open the bottle on the bottle label.

Each HETLIOZ LQ carton includes:

- 1 bottle of HETLIOZ LQ oral suspension
- 1 press-in bottle adapter
- A 5 mL oral dosing syringe. Always use the oral dosing syringe that comes with HETLIOZ LQ to measure your child’s prescribed dose.

(see Figure A)

Preparing a dose of HETLIOZ LQ:

Step 1. Remove the HETLIOZ LQ bottle, bottle adapter, and oral dosing syringe from the carton. Shake the bottle well for at least 30 seconds before each use (see Figure B).

Step 2. Press down on the child-resistant cap and twist the cap counterclockwise to open bottle (see Figure C).
Do not throw away the child-resistant cap.

Step 3. First time use only: Remove seal from bottle and insert press-in bottle adapter into the bottle. Press on the bottle adapter until it is even with the top of the bottle (see Figure D).
After the bottle adapter is in place, it should not be removed.

Step 4. First time use of bottle only: Replace child-resistant cap tightly by turning clockwise and shake well again for at least 30 seconds (see Figure E).

Step 5. Press down on the child-resistant cap and twist the cap counterclockwise to open bottle. Push plunger of oral dosing syringe completely down. Insert the oral dosing syringe into the opening of the press-in bottle adapter as far as it will go (see Figure F).

Step 6. With the oral dosing syringe in the bottle adapter, carefully turn the bottle upside down. Slowly pull back on the plunger to withdraw the prescribed amount of HETLIOZ LQ from the bottle. Line up the end of the plunger with the mL (milliliter) marking for your child’s prescribed dose of HETLIOZ LQ (see Figure G).

If you see more than a few air bubbles in the oral dosing syringe, fully push in the plunger so that the liquid flows back into the bottle. Repeat Step 6 until the air bubbles are mostly gone.

Step 7. Leave the oral dosing syringe in the bottle adapter and turn the bottle upright. Carefully remove the oral dosing syringe from the bottle adapter. Replace the child-resistant cap securely (see Figure H).

Step 8. Place the tip of the oral dosing syringe in the child’s mouth and toward the inside of their cheek. Slowly push the plunger all the way in to give the entire dose. Make sure the child has time to swallow the medicine (see Figure I).

Step 9. Remove the plunger from the barrel of the oral dosing syringe. Rinse the oral dosing syringe barrel and plunger with water (see Figure J). When the barrel and plunger are dry, put the plunger back into the oral dosing syringe.

Do not wash the oral dosing syringe in the dishwasher

Do not throw away the oral dosing syringe. Keep this oral dosing syringe for use with this bottle of HETLIOZ LQ.

Storing HETLIOZ LQ:

- Store HETLIOZ LQ in a refrigerator at 36°F to 46°F (2°C to 8°C).
- Keep HETLIOZ LQ and all medicines out of the reach of children.

Disposal of HETLIOZ LQ Suspension

Once opened, the 48 mL bottle can be stored for 5 weeks and the 158 mL bottle can be stored for 8 weeks, both at refrigerated temperature. Safely throw away any unused HETLIOZ LQ suspension after these time points. Ask your pharmacist how to properly throw away (dispose of) medicines you no longer use.

What are the ingredients in HETLIOZ LQ oral suspension?

Active ingredient: tasimelteon

Inactive ingredients: ascorbic acid, cherry flavor, mannitol, microcrystalline cellulose/carboxymethylcellulose sodium, polysorbate 80, sodium benzoate, sodium chloride, sucrose, sucralose, and water.

Distributed by:
Vanda Pharmaceuticals Inc. Washington, D.C. 20037 USA
www.hetlioz.com

Vanda and HETLIOZ LQ are trademarks or registered trademarks of Vanda Pharmaceuticals Inc. in the United States and other countries.

This Instructions for Use has been approved by the U.S. Food and Drug Administration.

Issued: December 2020